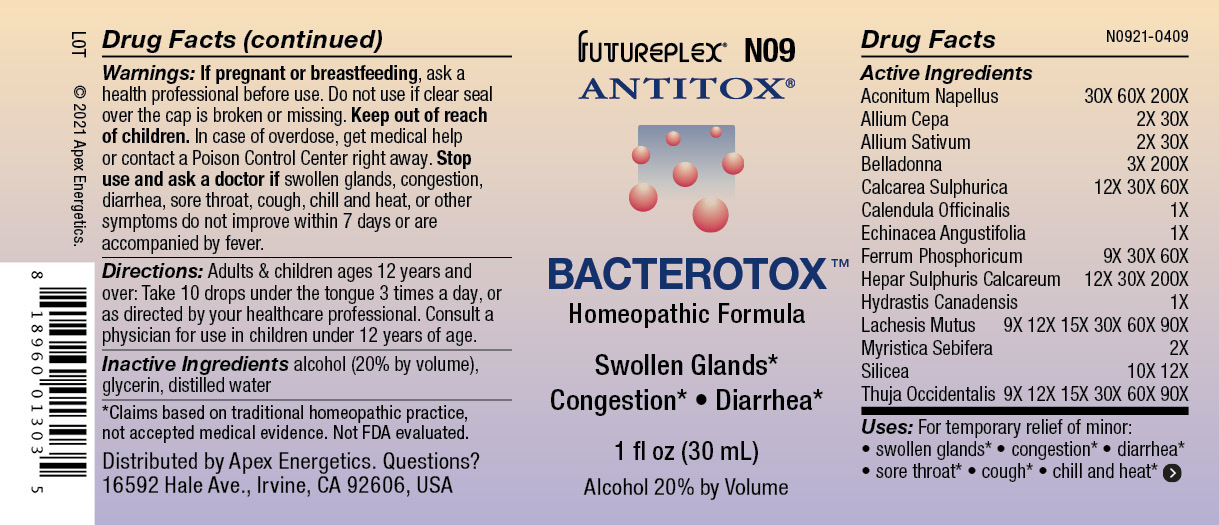 DRUG LABEL: N09
NDC: 63479-1409 | Form: SOLUTION/ DROPS
Manufacturer: Apex Energetics Inc.
Category: homeopathic | Type: HUMAN OTC DRUG LABEL
Date: 20240108

ACTIVE INGREDIENTS: SILICON DIOXIDE 12 [hp_X]/1 mL; ONION 30 [hp_X]/1 mL; CALENDULA OFFICINALIS FLOWERING TOP 1 [hp_X]/1 mL; ECHINACEA ANGUSTIFOLIA 1 [hp_X]/1 mL; CALCIUM SULFIDE 200 [hp_X]/1 mL; LACHESIS MUTA VENOM 90 [hp_X]/1 mL; FERROSOFERRIC PHOSPHATE 60 [hp_X]/1 mL; GOLDENSEAL 1 [hp_X]/1 mL; ACONITUM NAPELLUS 200 [hp_X]/1 mL; GARLIC 30 [hp_X]/1 mL; ATROPA BELLADONNA 200 [hp_X]/1 mL; VIROLA SEBIFERA RESIN 2 [hp_X]/1 mL; THUJA OCCIDENTALIS LEAFY TWIG 90 [hp_X]/1 mL; CALCIUM SULFATE ANHYDROUS 60 [hp_X]/1 mL
INACTIVE INGREDIENTS: ALCOHOL; GLYCERIN; WATER

N09

Active Ingredients
Aconitum Napellus | 30X 60X 200X
Allium Cepa | 2X 30X
Allium Sativum | 2X 30X
Belladonna | 3X 200X
Calcarea Sulphurica | 12X 30X 60X
Calendula Officinalis | 1X
Echinacea Angustifolia | 1X
Ferrum Phosphoricum | 9X 30X 60X
Hepar Sulphuris Calcareum | 12X 30X 200X
Hydrastis Canadensis | 1X
Lachesis Mutus | 9X 12X 15X 30X 60X 90X
Myristica Sebifera | 2X
Silicea | 10X 12X
Thuja Occidentalis | 9X 12X 15X 30X 60X 90X

INDICATIONS AND USAGE

Uses:

For temporary relief of minor:

swollen glands*

congestion*

diarrhea*

sore throat*

cough*

chill and heat*

*Claims based on traditional homeopathic practice, not accepted medical evidence. Not FDA evaluated.

Warnings:

PREGNANCY OR BREAST FEEDING

If pregnant or breastfeeding, ask a health professional before use.

Do not use if clear seal over the cap is broken or missing.

Keep out of reach of children. In case of overdose, get medical help or contact a Poison Control Center right away.

Stop use and ask a doctor if swollen glands, congestion, diarrhea, sore throat, cough, chill and heat, or other symptoms do not improve within 7 days or are accompanied by fever.

Directions:

Adults & children ages 12 years and over: Take 10 drops under the tongue 3 times a day, or as directed by your healthcare professional. Consult a physician for use in children under 12 years of age.

Inactive Ingredients

alcohol (20% by volume), glycerin, distilled water

Distributed by Apex Energetics. Questions?

16592 Hale Ave., Irvine, CA 92606, USA

PACKAGE LABEL

FUTUREPLEX® N09

ANTITOX®

BACTEROTOX™

Homeopathic Formula

Swollen Glands*

Congestion*

Diarrhea*

1 fl oz (30 mL)

Alcohol 20% by Volume